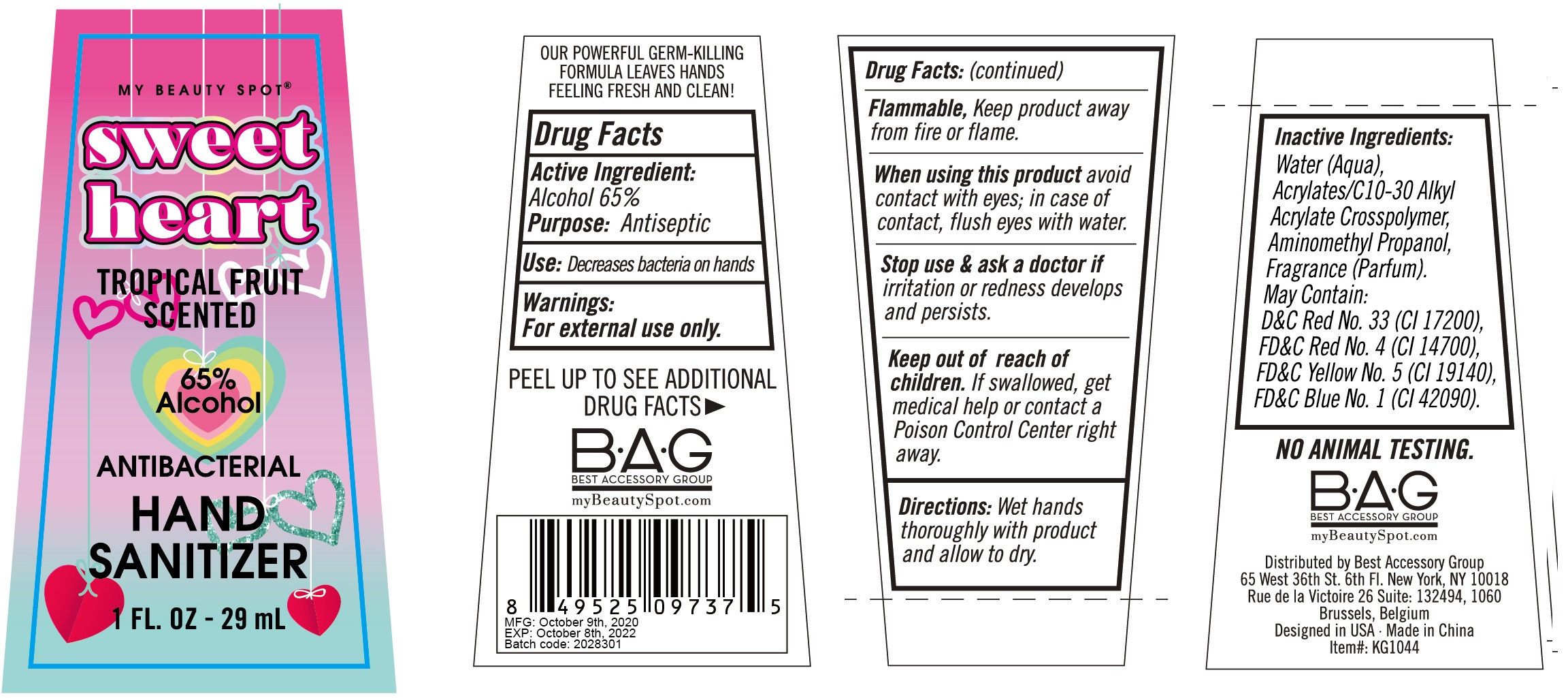 DRUG LABEL: Sweet Heart Antibacterial Hand Sanitizer Tropical Fruit Scented
NDC: 56136-058 | Form: GEL
Manufacturer: Ganzhou Olivee Cosmetic Co., Ltd.
Category: otc | Type: HUMAN OTC DRUG LABEL
Date: 20200828

ACTIVE INGREDIENTS: ALCOHOL 65 mL/100 mL
INACTIVE INGREDIENTS: WATER; CARBOMER COPOLYMER TYPE A; AMINOMETHYLPROPANOL; FD&C RED NO. 4

HAND SANITIZER

Active ingredient

Alcohol 65%

Purpose

Antiseptic

USE

Decrease bacteria on hands

WARNINGS

For external use only.

Flammable- Keep produt away from fire or flame.

When using this product Avoid contact with eyes; in case of contact, flush eyes with water.

Stop use and ask a doctor if irritation or redness develops and persists

KEEP OUT OF REACH OF CHILDREN

If swallowed, get medical help or contact a Poison Control Center right away

Directions

Wet hands thoroughly with product and allow to dry

Inactive ingredients

Water (Aqua), Acrylates/C10-30 Alkyl Acrylate Crosspolymer, Aminomethyl Propanol, Fragrance (Parfum). may contain: D&C Red No. 33 (Cl 17200), FD&C Red No. 4 (Cl 14700), FD & C Yellow No. 5 (Cl 19140), FD&C Blue No. 1 (Cl 42090).